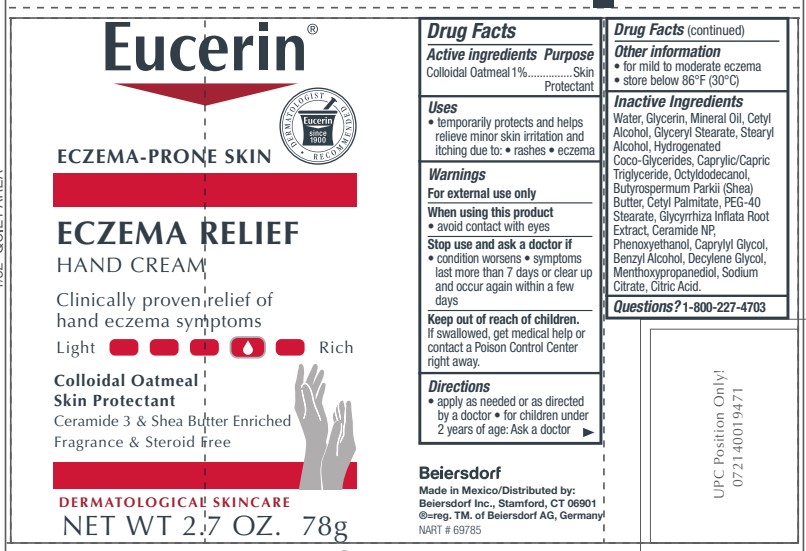 DRUG LABEL: Eucerin Eczema Relief Hand
NDC: 10356-375 | Form: CREAM
Manufacturer: Beiersdorf Inc
Category: otc | Type: HUMAN OTC DRUG LABEL
Date: 20241231

ACTIVE INGREDIENTS: OATMEAL 1 g/100 g
INACTIVE INGREDIENTS: GLYCERIN; WATER; MINERAL OIL; CETYL ALCOHOL; GLYCERYL MONOSTEARATE; MEDIUM-CHAIN TRIGLYCERIDES; OCTYLDODECANOL; CETYL PALMITATE; PEG-40 STEARATE; GLYCYRRHIZA INFLATA ROOT; CERAMIDE 3; PHENOXYETHANOL; CAPRYLYL GLYCOL; BENZYL ALCOHOL; CITRIC ACID MONOHYDRATE; 3-((L-MENTHYL)OXY)PROPANE-1,2-DIOL; DECYLENE GLYCOL; SHEA BUTTER; STEARYL ALCOHOL; HYDROGENATED COCO-GLYCERIDES; SODIUM CITRATE

Eucerin Eczema Relief Hand

Active ingredients
Colloidal Oatmeal 1%

Warnings
For external use only

When using this product avoid contact with eyes

Stop use and ask a doctor if
condition worsens
symptoms last more than 7 days or clear up and occur again within a few days

Keep out of reach of children. If swallowed, get medical help or
contact a Poison Control Center right away.

Uses
temporarily protects and helps relieve minor skin irritation and itching
due to rashes, eczema

Directions
Apply as needed or as directed by a doctor. For children under two years of age: Ask a doctor.

Questions or comments?
1-800-227-4703

PURPOSE

Skin protectant

Inactive Ingredients

Water, Glycerin, Mineral Oil, Cetyl Alcohol, Glyceryl Stearate, Stearyl Alcohol, Hydrogenated Coco-Glycerides, Caprylic/Capric Triglyceride, Octyldodecanol, Butyrospermum Parkii (Shea) Butter, Cetyl Palmitate, PEG-40 Stearate, Glycyrrhiza Inflata Root Extract, Ceramide NP, Phenoxyethanol, Caprylyl Glycol, Benzyl Alcohol, Decylene Glycol, Menthoxypropanediol, Sodium Citrate, Citric Acid.

PACKAGE LABEL

Eucerin Eczema Relief Hand Cream

Eczema-Prone Skin

Colloidal Oatmeal Skin Protectant

Clinically proven relief of hand eczema symptoms

Ceramide 3 and Shea Butter Enriched

Fragrance and Steroid Free

Dermatological skincare